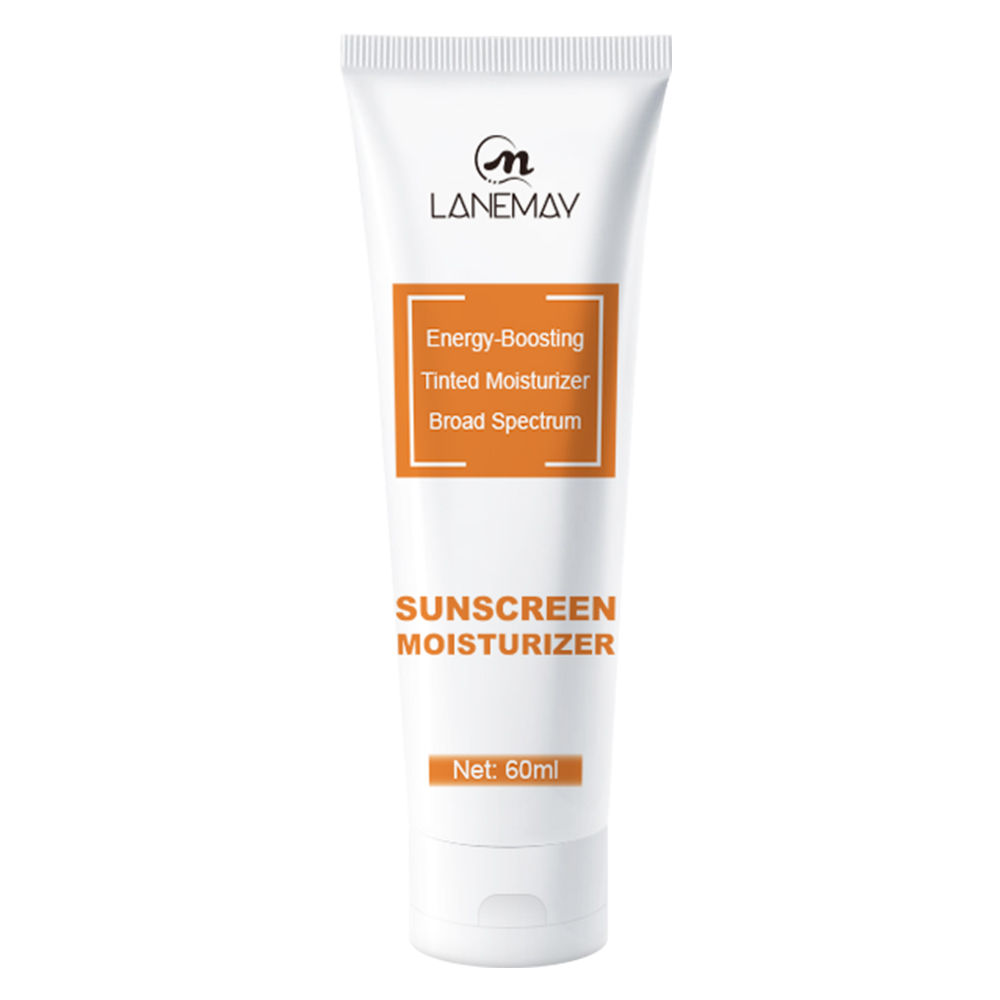 DRUG LABEL: SUNSCREEN MOISTURIZER
NDC: 84025-135 | Form: CREAM
Manufacturer: Guangzhou Yanxi Biotechnology Co., Ltd
Category: otc | Type: HUMAN OTC DRUG LABEL
Date: 20240125

ACTIVE INGREDIENTS: ZINC OXIDE 35 mg/1 mL
INACTIVE INGREDIENTS: WATER

WARNINGS

For external use only.keep out of reach of children.Avoid contact with eyes.Discontinue use if signs of irritation or rash occur.Store in a cool and dry place.

INDICATIONS AND USAGE

Many different skin types.